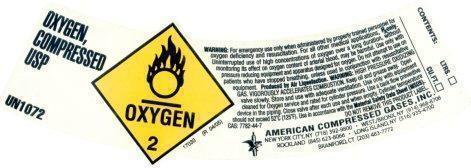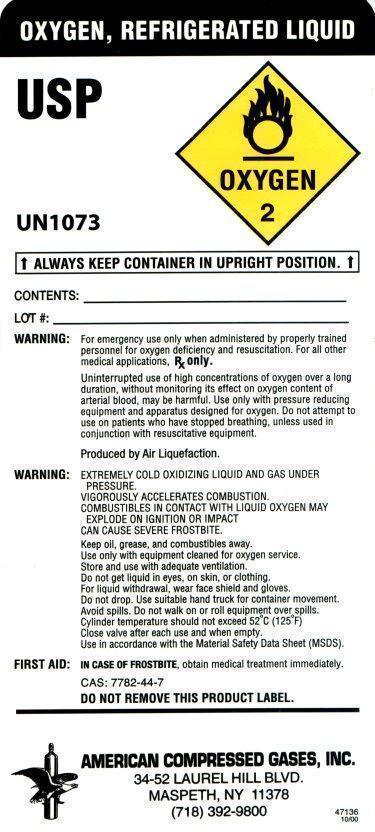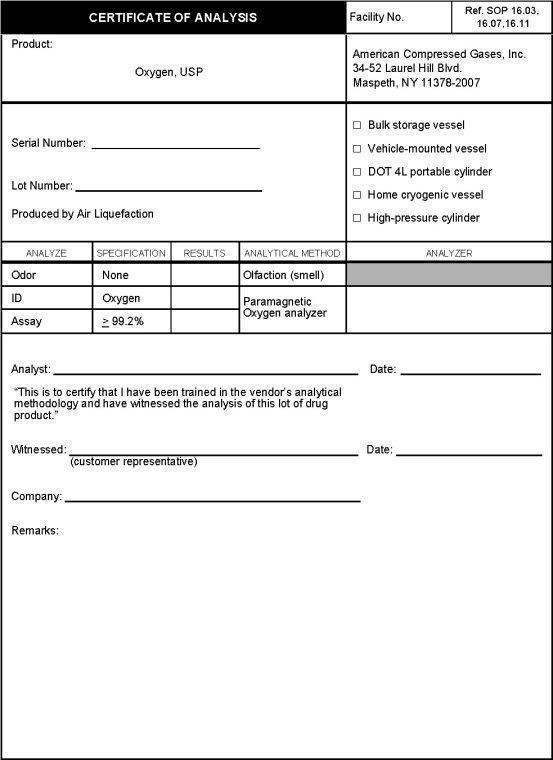 DRUG LABEL: Oxygen
NDC: 49496-001 | Form: GAS
Manufacturer: American Compressed Gases Inc.
Category: prescription | Type: HUMAN PRESCRIPTION DRUG LABEL
Date: 20181102

ACTIVE INGREDIENTS: OXYGEN 992 mL/1 L

Oxygen, compressed

OXYGEN, COMPRESSED USP
UN 1072
WARNING: For emergency use only when administered by properly trained personnel for oxygen deficiency and resuscitation. For all other medical applications, Rx only. Uninterrupted use of high concentrations of oxygen over a long duration, without monitoring its effect on oxygen content of arterial blood, may be harmful. Use only with pressure reducing equipment and apparatus designed for oxygen. Do not attempt to use on patients who have stopped breathing, unless used in conjunction with resuscitative equipment. Produced by Air Liquefaction. WARNING: HIGH PRESSURE OXIDIZING GAS. VIGOROUSLY ACCELERATES COMBUSTION. Keep oil and grease away. Open valve slowly. Store and use with adequate ventilation. Use only with equipment cleaned for Oxygen service and rated for cylinder pressure. Use a backflow preventive device in the piping. Close valve after each use and when empty. Cylinder temperature should not exceed 52oC (125oF). Use in accordance with the Material Safety Data Sheet (MSDS).
CAS:7782-44-7
DO NOT REMOVE THIS PRODUCT LABEL
AMERICAN COMPRESSED GASES, INC.
NEW YORK CITY, NY (718) 392-9800 . WEST/BRONX, NY (914) 968-8708
ROCKLAND (845) 623-8066 . LONG ISLAND, NY (516) 935-4700
BRANFORD, CT (203) 483-7772
17033 (R 04/05)

CONTENTS: LTRS._____ CU.FT. _____

OXYGEN, REFRIGERATED LIQUID USP
UN 1073
ALWAYS KEEP CONTAINER IN UPRIGHT POSITIO N
WARNING: For emergency use only when administered by properly trained personnel for oxygen deficiency and resuscitation. For all other medical applications, Rx only.
Uninterrupted use of high concentrations of oxygen over a long duration, without monitoring its effect on oxygen content of arterial blood, may be harmful. Use only with pressure reducing equipment and apparatus designed for oxygen. Do not attempt to use on patients who have stopped breathing, unless used in conjunction with resuscitative equipment.
Produced by Air Liquefaction.
WARNING: EXTREMELY COLD OXIDIZING LIQUID AND GAS UNDER PRESSURE. VIGOROUSLY ACCELERATES COMBUSTION. COMBUSTIBLES IN CONTACT WITH LIQUID OXYGEN MAY EXPLODE ON IGNITION OR IMPACT. CAN CAUSE SEVERE FROSTBITE.
Keep oil, grease, and combustibles away. Use only with equipment cleaned for oxygen service. Store and use with adequate ventilation. Do not get liquid in eyes, on skin, or clothing. For liquid withdrawal, wear face shield and gloves. Do not drop. Use suitable hand truck for container movement. Avoid spills. Do not walk on or roll equipment over spills. Cylinder temperature should not exceed 52oC (125oF). Close valve after each use and when empty. Use in accordance with the Material Safety Data Sheet (MSDS).
FIRST AID: IN CASE OF FROSTBITE, obtain medical treatment immediately.
CAS:7782-44-7
DO NOT REMOVE THIS PRODUCT LABEL
AMERICAN COMPRESSED GASES, INC.
34-52 LAUREL HILL BLVD.
MASPETH, NY 11378
(718) 392-9800
47136 (10/00)

Oxygen, certificate of analysis

CERTIFICATE OF ANALYSIS Facility No. Ref. SOP 16.03, 16.07, 16.11
Product: Oxygen, USP American Compressed Gases, Inc. 34-52 Laurel Hill Blvd. Maspeth, NY 11378-2007
Serial No.__________
Lot No. __________
Produced by Air Liquefaction
[ ] Bulk storage vessel [ ] Vehicle-mounted vessel [ ] DOT 4L portable cylinder [ ] Home cryogenic vessel [ ] High-pressure cylinder

ANALYZE SPECIFICATION RESULTS ANALYTICAL METHOD ANALYZER
Odor None _______ Olfaction (smell)
ID Oxygen _______ Paramagnetic Oxygen analyzer
Assay >99.2 _______

Analyst ____________ Date:_______
“This is to certify that I have been trained in the vendor’s analytical methodology and have witnessed the analysis of this lot of drug product”
Witnessed: ____________ (Customer representative) Date: _______
Company:_____________
Remarks: